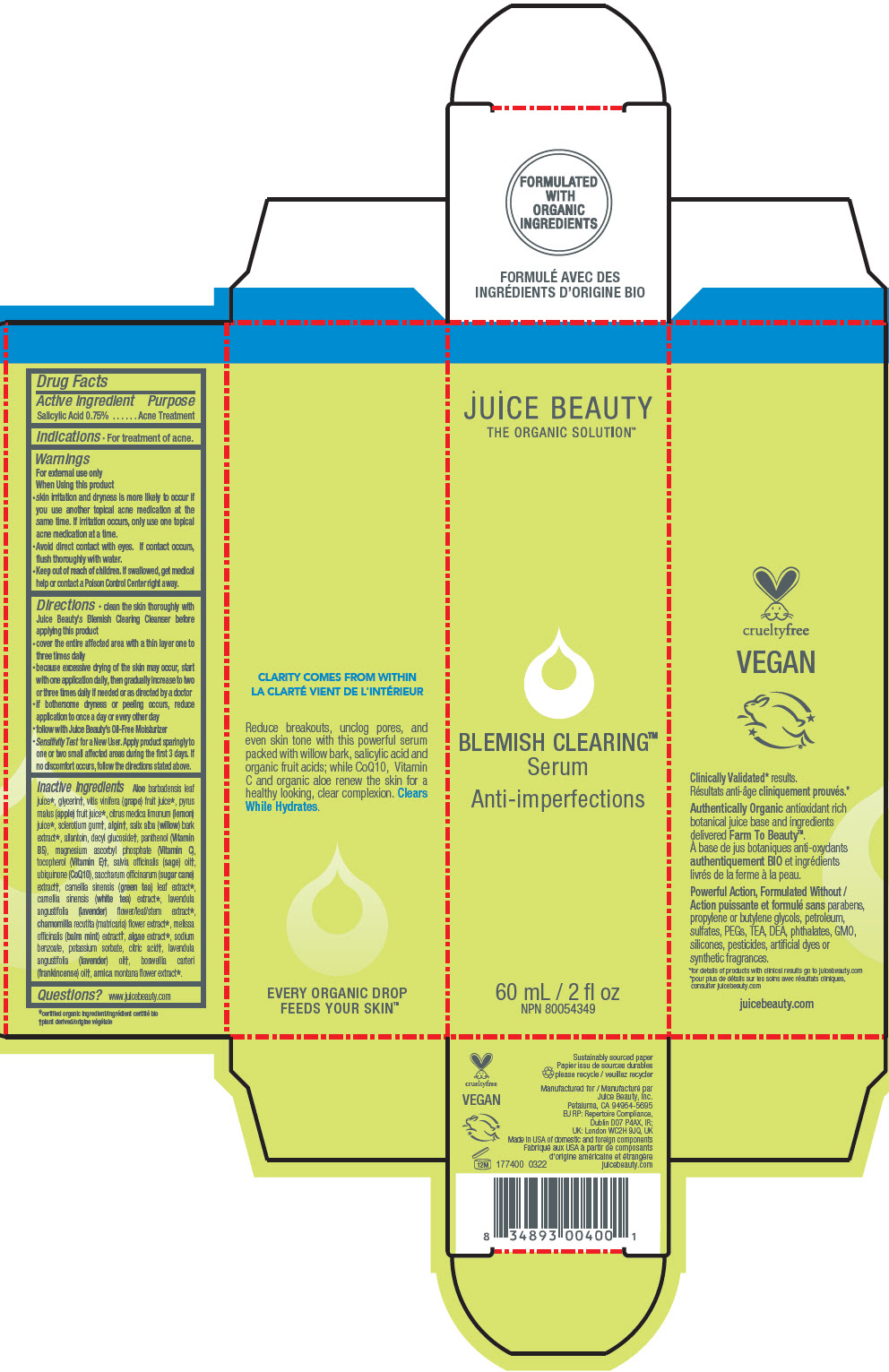 DRUG LABEL: Blemish serum
NDC: 55165-0106 | Form: LOTION
Manufacturer: Juice Beauty
Category: otc | Type: HUMAN OTC DRUG LABEL
Date: 20241223

ACTIVE INGREDIENTS: Salicylic acid 0.75 g/100 mL
INACTIVE INGREDIENTS: ALOE VERA LEAF; glycerin; WINE GRAPE JUICE; APPLE JUICE; LEMON JUICE; BETASIZOFIRAN; SODIUM ALGINATE; SALIX ALBA BARK; allantoin; decyl glucoside; PANTHENOL; MAGNESIUM ASCORBYL PHOSPHATE; TOCOPHEROL; SAGE OIL; UBIDECARENONE; SUGARCANE; GREEN TEA LEAF; WHITE TEA; LAVANDULA ANGUSTIFOLIA SUBSP. ANGUSTIFOLIA FLOWERING TOP; CHAMOMILE; MELISSA OFFICINALIS WHOLE; LAMINARIA DIGITATA; sodium benzoate; potassium sorbate; CITRIC ACID MONOHYDRATE; LAVENDER OIL; FRANKINCENSE OIL; ARNICA MONTANA FLOWER

Blemish serum

Drug Facts

Active Ingredient

Salicylic Acid 0.75%

Purpose

Acne Treatment

Indications

- For treatment of acne.

Warnings

For external use only

When Using this product

- skin irritation and dryness is more likely to occur if you use another topical acne medication at the same time. If irritation occurs, only use one topical acne medication at a time.
- Avoid direct contact with eyes. If contact occurs, flush thoroughly with water.

- Keep out of reach of children. If swallowed, get medical help or contact a Poison Control Center right away.

Directions

- clean the skin thoroughly with Juice Beauty's Blemish Clearing Cleanser before applying this product
- cover the entire affected area with a thin layer one to three times daily
- because excessive drying of the skin may occur, start with one application daily, then gradually increase to two or three times daily if needed or as directed by a doctor
- if bothersome dryness or peeling occurs, reduce application to once a day or every other day
- follow with Juice Beauty's Oil-Free Moisturizer
- Sensitivity Test for a New User. Apply product sparingly to one or two small affected areas during the first 3 days. If no discomfort occurs, follow the directions stated above.

Inactive Ingredients

Aloe barbadensis leaf juice [certified organic ingredient] , glycerin [plant derived] , vitis vinifera (grape) fruit juice, pyrus malus (apple) fruit juice, citrus medica limonum (lemon) juice, sclerotium gum, algin, salix alba (willow) bark extract, allantoin, decyl glucoside, panthenol (Vitamin B5), magnesium ascorbyl phosphate (Vitamin C), tocopherol (Vitamin E), salvia officinalis (sage) oil, ubiquinone (CoQ10), saccharum officinarum (sugar cane) extract, camellia sinensis (green tea) leaf extract, camellia sinensis (white tea) extract, lavendula angustifolia (lavender) flower/leaf/stem extract, chamomilla recutita (matricaria) flower extract, melissa officinalis (balm mint) extract, algae extract, sodium benzoate, potassium sorbate, citric acid, lavendula angustifolia (lavender) oil, boswellia carteri (frankincense) oil, arnica montana flower extract.

Questions?

www.juicebeauty.com

PRINCIPAL DISPLAY PANEL - 60 mL Bottle Carton

JUICE BEAUTY
THE ORGANIC SOLUTION™

BLEMISH CLEARING™
Serum

Anti-imperfections

60 mL / 2 fl oz
NPN 80054349